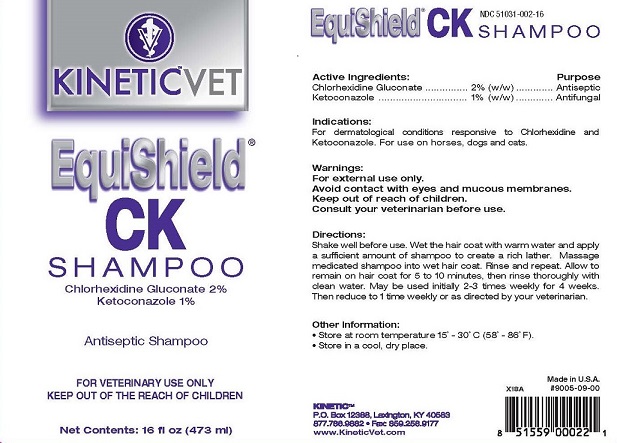 DRUG LABEL: EquiShield CK
NDC: 51031-002 | Form: SHAMPOO
Manufacturer: Kinetic Technologies, LLC
Category: animal | Type: OTC ANIMAL DRUG LABEL
Date: 20211011

ACTIVE INGREDIENTS: CHLORHEXIDINE GLUCONATE 2 g/100 mL; KETOCONAZOLE 1 g/100 mL

EquiShield® CK Shampoo

Active Ingredients: Purpose:

Chlorhexidine Gluconate 2% (w/w) .......... Antiseptic

Ketoconazole 1% (w/w) ......................... Antifungal

Indications:

For dermatological conditions reponsive to Chlorhexidine and Ketoconazole. For use on horses, dogs and cats.

Warnings:

For external use only.

Avoid contact with eyes and mucous membranes.

Keep out of reach of children.

Consult your veterinarian before use.

Directions:

Shake well before use. Wet the hair coat with warm water and apply a sufficient amount of shampoo to create a rich lather. Massage medicated shampoo into wet hair coat. Rinse and repeat. Allow to remain on hair coat for 5 to 10 minutes, then rinse thoroughly with clean water. May be used initially 2-3 times weekly for 4 weeks. Then reduce to 1 time weekly or as directed by your veterinarian.

Other Information:

- Store at room temperature 15° - 30° C (58° - 86 F).
- Store in a cool, dry place.

Made in the U.S.A.

#9005-09-00

#9005-09-01

KINETIC™

P.O. Box 12388, Lexington, KY 40583

877.786.9882 • Fax: 859.258.9177

www.KineticVet.com

KINETIC™VET

EquiShield® CK SHAMPOO

Chlorhexidine Gluconate 2%

Ketoconazole 1%

Antiseptic Shampoo

FOR VETERINARY USE ONLY

KEEP OUT OF THE REACH OF CHILDREN

Net Contents: 16 fl oz (473 ml)